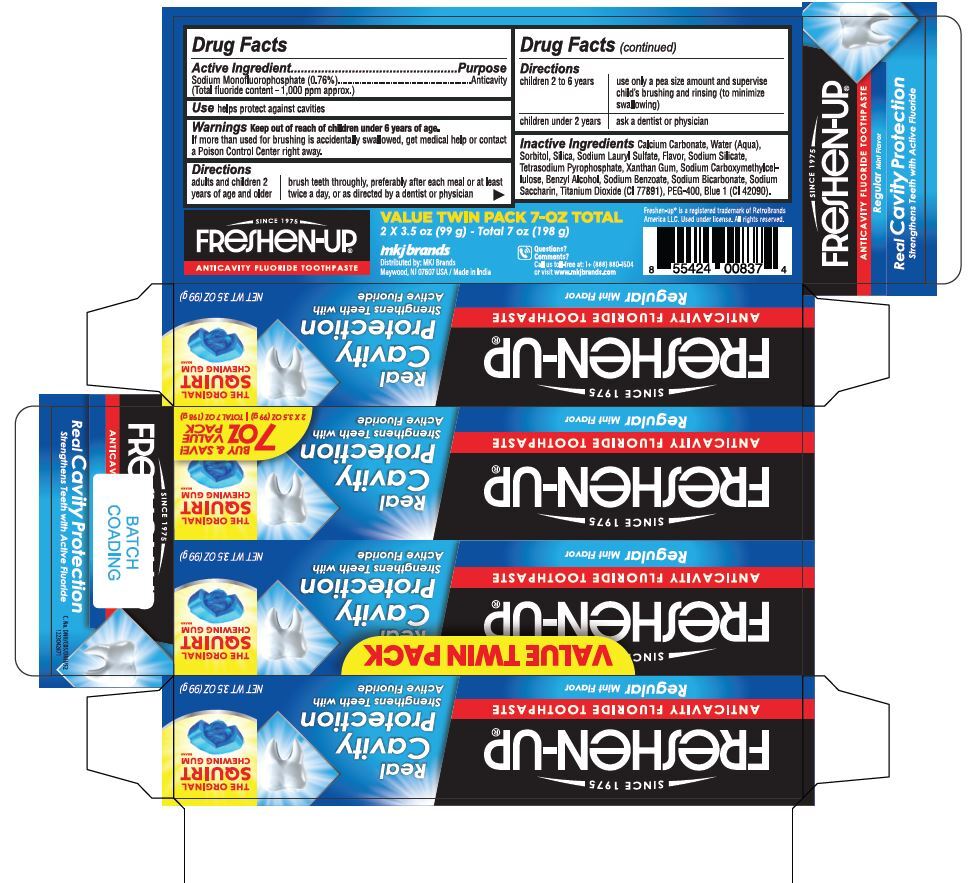 DRUG LABEL: Freshen Up
NDC: 77782-005 | Form: GEL, DENTIFRICE
Manufacturer: MKJ BRANDS LLC
Category: otc | Type: HUMAN OTC DRUG LABEL
Date: 20260102

ACTIVE INGREDIENTS: SODIUM MONOFLUOROPHOSPHATE 0.76 g/100 g
INACTIVE INGREDIENTS: BENZYL ALCOHOL; SODIUM LAURYL SULFATE; SODIUM SACCHARIN; SORBITOL; WATER; HYDRATED SILICA; PEG-400; XANTHAN GUM; TETRASODIUM PYROPHOSPHATE; CARBOXYMETHYLCELLULOSE SODIUM; SODIUM SILICATE; TITANIUM DIOXIDE; CI 42090

Freshen-up Real Cavity protection

Drug Facts

Active ingredient

Sodium Monofluorophosphate (0.76%)........Anticavity

Total Fluoride content- 1000 ppm appx.

Purpose

Anticavity

Use

helps protect against cavities

Warnings

Stop use and ask a dentist if the problem persists or worsens, snesitive teeth may indicate a serious problem that may need prompt care by dentist. Pain senstivity still persists after 4 weeks of use

Keep out of reach of children under 6 years of age.If more than used for brushing is accidentally swallowed, get medical help or contact a Poison Control Center right away.

Directions

adults and children 2 years of age and older | brush teeth thoroughly, preferably after each meal or at least twice a day or as directed by physician or dentist
children 2 to 6 years | use only a pea siz amount and supervise child's brushing and rinsing (to minimize swallowing)
children under 2 years | ask a dentist or physician

Inactive ingredients

calcium carbonate, water, sorbitol, silica, SLS, flavor, sodium silicate, tetrasodium pyrophosphate, xanthum gum, sodium carboxymethylcellulose, benzyl alcohol, sodium benzoate, sodium bicarbonate, sodium saccharin, titanium dioxide, peg-400, blue 1

Questions?

1-888-880-1504

Dist. by:
MKJ Brands